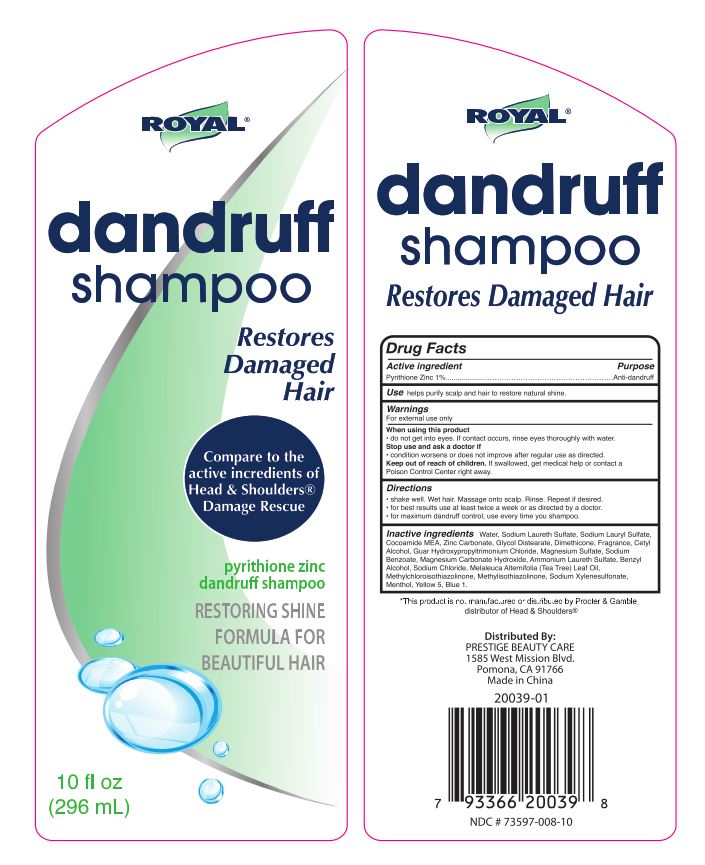 DRUG LABEL: Royal Dandruff
NDC: 73597-008 | Form: SHAMPOO
Manufacturer: Mission Series Inc. dba Prestige Beauty Care
Category: otc | Type: HUMAN OTC DRUG LABEL
Date: 20200519

ACTIVE INGREDIENTS: PYRITHIONE ZINC 1 g/100 g
INACTIVE INGREDIENTS: SODIUM LAURETH SULFATE; SODIUM LAURYL SULFATE; SODIUM XYLENESULFONATE; ZINC CARBONATE; GLYCOL DISTEARATE; DIMETHICONE; CETYL ALCOHOL; GUAR HYDROXYPROPYLTRIMONIUM CHLORIDE (1.7 SUBSTITUENTS PER SACCHARIDE); MENTHOL; FD&C YELLOW NO. 5; FD&C BLUE NO. 1; METHYLISOTHIAZOLINONE; METHYLCHLOROISOTHIAZOLINONE; TEA TREE OIL; WATER; COCO MONOETHANOLAMIDE; BENZYL ALCOHOL; AMMONIUM LAURYL SULFATE; SODIUM CHLORIDE

Royal Dandruff

Active Ingredient

Active Ingredient - Pyrithione Zinc 1%

Purpose

Purpose - Anti-dandruff

Use

Use - helps purify scalp and hair to restore natural shine.

Warnings

Warnings - For external use only.

Warnings

Warnings - For external use only.

When using this product

- do not get into eyes. If contact occurs, rinse eyes thoroughly with water.

Stop Use

Stop use and ask a doctor if

- condition worsens or does not improve after regular use as directed.

Keep out of reach of children. If swallowed, get medical help or contact a Poison Control Center right away.

Directions

- shake well. Wet hair. Massage onto scalp. Rinse. Repeat if desired.

- for best results use at least twice a week or as directed by a doctor.

- for maximum dandruff control, use every time you shampoo.

Inactive Ingredients

Inactive Ingredients - Water, Sodium Laureth Sulfate, Sodium Lauryl Sulfate, Cocoamide MEA, Zinc Carbonate, Glycol Distearate, Dimethicone, Cetyl Alcohol, Guar Hydroxypropyltrimonium Chloride, Magnesium Sulfate, Sodium Benzoate, Magnesium Carbonate Hydroxide, Ammonium Laureth Sulfate, Benzyl Alcohol, Sodium Chloride, Melaleuca Alternifolia (Tea Tree) Leaf Oil, Methylchloroisothiazolinone, Methylisothiazolinone, Sodium Xylenesulfonate, Menthol, Yellow 5, Blue 1.

Distributed By

PRESTIGE BEAUTY CARE

1585 West Mission Blvd.

Pomona, CA 91766

Made in China